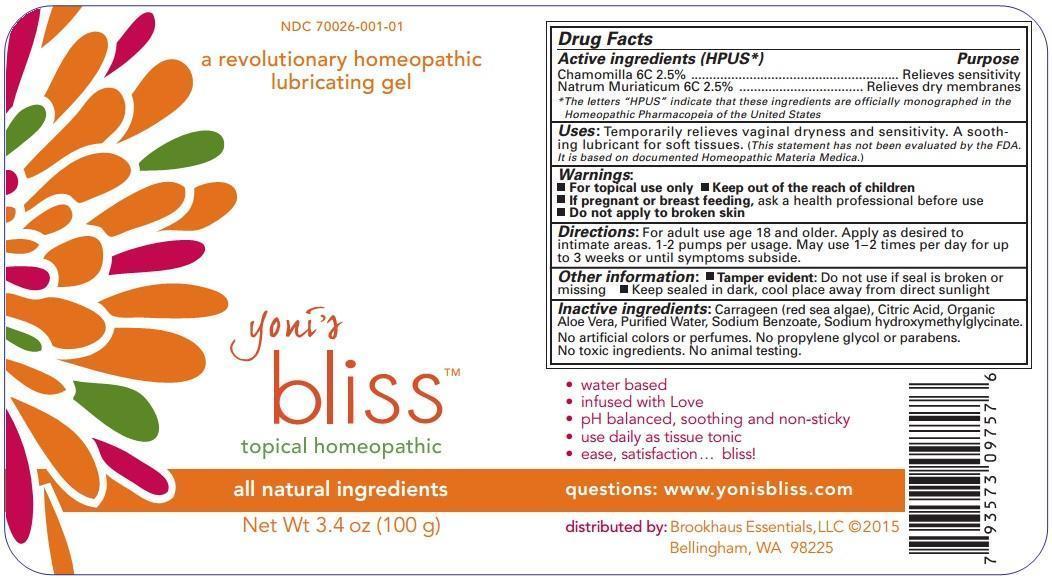 DRUG LABEL: Yonis Bliss
NDC: 70026-001 | Form: GEL
Manufacturer: Brookhaus Essentials LLC
Category: homeopathic | Type: HUMAN OTC DRUG LABEL
Date: 20221130

ACTIVE INGREDIENTS: MATRICARIA RECUTITA 6 [hp_C]/1 g; SODIUM CHLORIDE 6 [hp_C]/1 g
INACTIVE INGREDIENTS: CARRAGEENAN; CITRIC ACID MONOHYDRATE; ALOE VERA LEAF; WATER; SODIUM BENZOATE; SODIUM HYDROXYMETHYLGLYCINATE

yoni's bliss

Active ingredients (HPUS*) | Purpose
Chamomilla 6C 2.5% | Relieves sensitivity
Natrum Muriaticum 6C 2.5% | Relieves dry membranes

OTHER SAFETY INFORMATION

*The letters "HPUS" indicate that these ingredients are officially monographed in the Homeopathic Pharmacopeia of the United States.

INDICATIONS AND USAGE

Uses: Temporarily relieves vaginal dryness and sensitivity. A soothing lubricant for soft tissues.

(This statement has not been evaluated by the FDA. It is based on documented Homeopathic Materia Medica.)

Warnings:

- For topical use only
- Keep out of the reach of children
- If pregnant or breast-feeding, ask a health professional before use
- Do not apply to broken skin

Keep out of the reach of children

DOSAGE AND ADMINISTRATION

Directions: For adult use age 18 and older. Apply as desired to intimate areas. 1-2 pumps per usage. May use 1-2 times per day for up to 3 weeks or until symptoms subside.

Other information:

- Tamper evident. Do not use if seal is broken or missing
- Keep sealed in dark, cool place away from direct sunlight

INACTIVE INGREDIENT

Inactive ingredients: Carrageenan (red sea algae), Citric Acid, Organic Aloe Vera, Purified Water, Sodium Benzoate, Sodium Hydroxymethylglycinate.

No artificial colors or perfumes. No propylene glycol or parabens. No toxic ingredients. No animal testing.

questions: www.yonisbliss.com

distributed by: Brookhaus Essentials, LLC

Bellingham, WA 98225

OTHER SAFETY INFORMATION

- water based
- infused with Love
- pH balanced, soothing and non-sticky
- use daily as tissue tonic
- ease, satisfaction... bliss!

PURPOSE

a revolutionary homeopathic lubricating gel

PACKAGE LABEL

NDC 70026-001-01

a revolutionary homeopathic lubricating gel

yoni's bliss

topical homeopathic

all natural ingredients

Net Wt 3.4 oz (100 g)